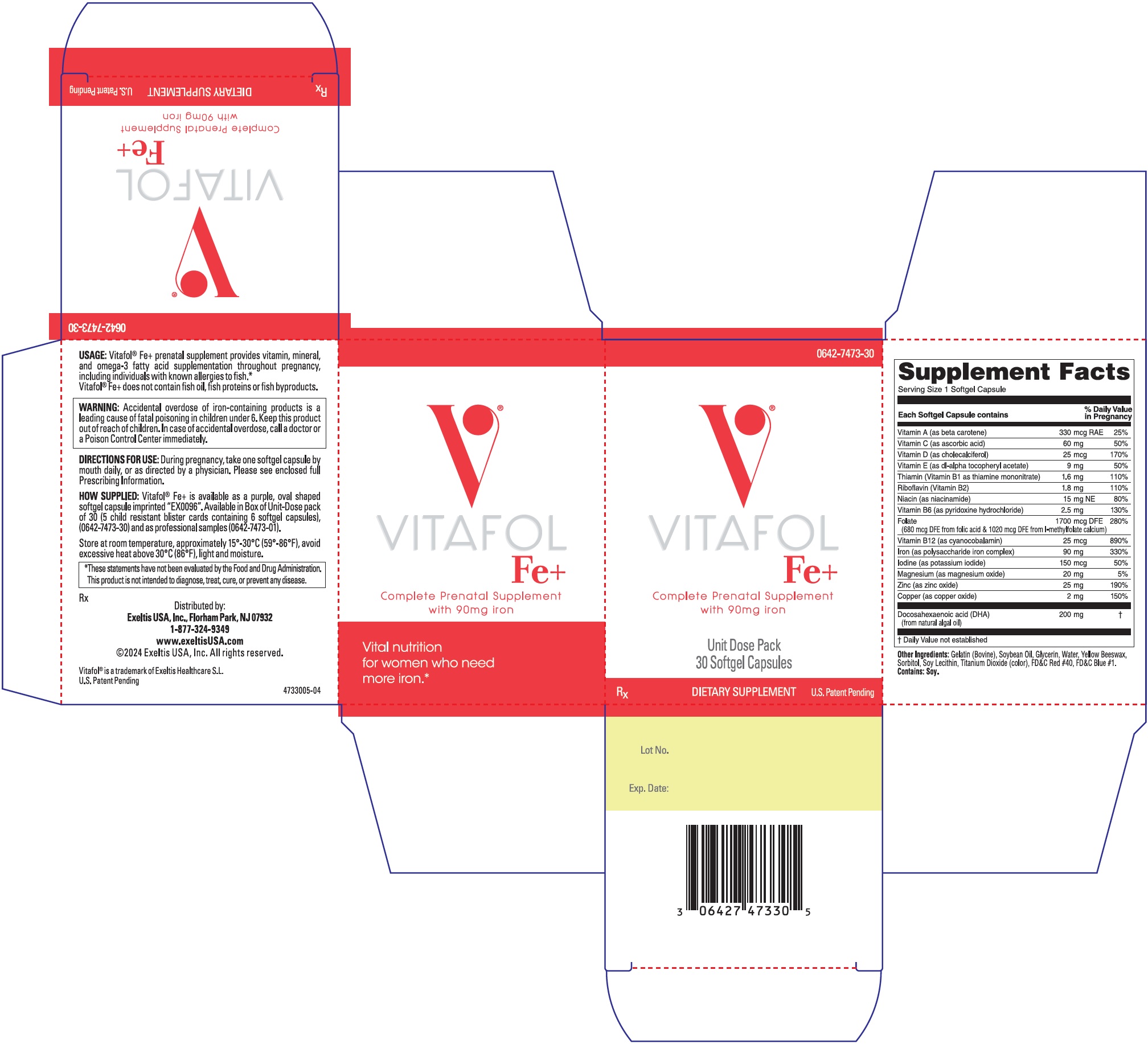 DRUG LABEL: Vitafol Fe Plus
NDC: 0642-7473 | Form: CAPSULE, LIQUID FILLED
Manufacturer: Exeltis USA, Inc.
Category: prescription | Type: HUMAN PRESCRIPTION DRUG LABEL
Date: 20250320

ACTIVE INGREDIENTS: DOCONEXENT 200 mg/1 1; NIACINAMIDE 15 mg/1 1; .ALPHA.-TOCOPHEROL ACETATE, DL- 9 mg/1 1; CHOLECALCIFEROL 25 mg/1 1; BETA CAROTENE 330 ug/1 1; ASCORBIC ACID 60 mg/1 1; THIAMINE MONONITRATE 1.6 mg/1 1; RIBOFLAVIN 1.8 mg/1 1; PYRIDOXINE HYDROCHLORIDE 2.5 mg/1 1; CYANOCOBALAMIN 25 ug/1 1; IRON 90 mg/1 1; ZINC OXIDE 25 mg/1 1; CUPRIC OXIDE 2 mg/1 1; POTASSIUM IODIDE 150 ug/1 1; MAGNESIUM OXIDE 20 mg/1 1; FOLIC ACID 680 mg/1 1; LEVOMEFOLATE CALCIUM 1020 ug/1 1
INACTIVE INGREDIENTS: GELATIN, UNSPECIFIED; SORBITOL; GLYCERIN; WATER; YELLOW WAX; SOYBEAN OIL; LECITHIN, SOYBEAN; TITANIUM DIOXIDE; FD&C BLUE NO. 1; FD&C RED NO. 40

0642-7473-30
Vitafol® Fe^+ Supplement
Prenatal Supplement with 90 mg Iron
Rx

COMPOSITION:

Each Vitafol® Fe+ softgel capsule contains:

Vitamin A (as beta carotene) | 330 mcg RAE
Vitamin C (as ascorbic acid) | 60 mg
Vitamin D (as cholecalciferol) | 25 mcg
Vitamin E (as dl-alpha tocopheryl acetate) | 9 mg
Thiamin (Vitamin B1 as thiamine mononitrate) | 1.6 mg
Riboflavin (Vitamin B2) | 1.8 mg
Niacin (as niacinamide) | 15 mg NE
Vitamin B6 (as pyridoxine hydrochloride) | 2.5 mg
Folate | 1700 mcg DFE
(680 mcg DFE from folic acid & 1020 mcg DFE from l-methylfolate calcium)
Vitamin B12 (as cyanocobalamin) | 25 mg
Iron (as polysaccharide iron complex) | 90 mg
Iodine (as potassium iodide) | 150 mcg
Magnesium (as magnesium oxide) | 20 mg
Zinc (as zinc oxide) | 25 mg
Copper (as copper oxide) | 2 mg
Docosahexaenoic acid (DHA); (from natural algal oil) | 200 mg

Other Ingredients:

Gelatin (Bovine), Soybean Oil, Glycerin, Yellow Beeswax, Sorbitol, Soy Lecithin, Titanium Dioxide (color), FD&C Red #40, FD&C Blue #1

Contains: Soy

USAGE:

Vitafol® Fe^+ prenatal supplement provides vitamin, mineral and omega-3 fatty acid supplementation throughout pregnancy, including individuals with known allergies to fish.* Vitafol® Fe^+ does not contain fish oils, fish proteins, or fish by-products.

CONTRAINDICATIONS:

Vitafol® Fe^+ prenatal supplement is contraindicated in patients with hypersensitivity to any of its components or color additives.

Folic acid is contraindicated in patients with untreated and uncomplicated pernicious anemia, and in those with anaphylactic sensitivity to folic acid.

Iron supplementation is contraindicated in patients with hemochromatosis and patients with iron storage disease or the potential for iron storage disease due to chronic hemolytic anemia (e.g., inherited anomalies of hemoglobin structure or synthesis and/or red cell enzyme deficiencies, etc.), pyridoxine responsive anemia, or cirrhosis of the liver.

Cyanocobalamin is contraindicated in patients with sensitivity to cobalt or to cyanocobalamin (vitamin B12).

WARNING:

Accidental overdose of iron-containing products is a leading cause of fatal poisoning in children under 6. Keep this product out of reach of children. In case of accidental overdose, call a doctor or a Poison Control Center immediately.

WARNINGS/PRECAUTIONS:

This product is intended for use as directed by your healthcare provider. Do not share with others. Vitafol® Fe^+ must be used with caution in patients with known sensitivity or allergy to soy.

Vitamin D supplementation should be used with caution in those with hypercalcemia or conditions that may lead to hypercalcemia such as hyperparathyroidism and those who form calcium-containing kidney stones. High doses of vitamin D can lead to elevated levels of calcium that reside in the blood and soft tissues. Bone pain, high blood pressure, formation of kidney stones, renal failure, and increased risk of heart disease can occur.

Iodine should be used with caution in patients with an overactive thyroid.

Prolonged use of iron salts may produce iron storage disease.

Folic acid, especially in doses above 0.1 mg daily, may obscure pernicious anemia, in that hematologic remission may occur while neurological manifestations remain progressive. The use of folic acid doses above 1 mg daily may precipitate or exacerbate the neurological damage of vitamin B12 deficiency.

Consumption of more than 3 grams of omega-3 fatty acids per day from all sources may lead to excessive bleeding. Supplemental intake of omega-3 fatty acids such as DHA exceeding 2 grams per day is not recommended.

Avoid Overdosage. Keep out of the reach of children.

DRUG INTERACTIONS

Medications for an overactive thyroid (anti-thyroid drugs) used in conjunction with iodine supplementation may lead to hypothyroidism.

Medications for hypertension used in conjunction with iodine supplementation may increase potassium levels in blood.

High doses of folic acid may result in decreased serum levels of the anticonvulsant drugs; carbamazepine, fosphenytoin, phenytoin, phenobarbital, valproic acid. Folic acid may decrease a patient's response to methotrexate.

Vitamin D supplementation should not be given with large amounts of calcium in those with hypercalcemia or conditions that may lead to hypercalcemia such as hyperparathyroidism and those who form calcium-containing kidney stones.

Zinc can inhibit the absorption of certain antibiotics; take at least 2 hours apart to minimize interactions.

Consult appropriate references for additional specific vitamin-drug interactions

INFORMATION FOR PATIENTS

Patients should be counseled to disclose all medical conditions, including use of all medications, vitamins and supplements, pregnancy, and breast-feeding.

PEDIATRIC USE

Not for pediatric use.

ADVERSE REACTIONS:

Adverse reactions have been reported with specific vitamins and minerals, but generally at doses substantially higher than those in Vitafol® Fe^+. However, allergic and idiosyncratic reactions are possible at any dose. Reported adverse events include skin ailments, gastrointestinal complaints, glucose abnormalities, and visual problems.

You should call your doctor for medical advice about adverse or unexpected reactions. To report to the company an adverse event or obtain product information, call 1-877-324-9349.

DOSAGE AND ADMINISTRATION:

Take one softgel capsule by mouth daily during pregnancy, or as directed by a physician.

HOW SUPPLIED:

Vitafol® Fe^+ is available as a purple, oval shaped softgel capsule imprinted "EX0096". Available in box of Unit-Dose pack of 30 (5 child resistant blister cards containing 6 softgel capsules) (0642-7473-30) and as professional samples (0642-7473-01).

STORAGE AND HANDLING

Store at room temperature, approximately 15°-30°C (59°-86°F), avoid excessive heat above 30°C (86°F), light and moisture.

*These statements have not been evaluated by the Food and Drug Administration. This product is not intended to diagnose, treat, cure, or prevent any disease.

Rx

Distributed by:

Exeltis USA, Inc.
Florham Park, NJ 07932
1-877-324-9349
www.exeltisusa.com
©2024 Exeltis USA, Inc. All rights reserved.

Vitafol® is a trademark of Exeltis Healthcare S.L.
4733001-05 July 2024

PRINCIPAL DISPLAY PANEL - 30 Capsule Dose Pack Box

0642-7473-30

VITAFOL
Fe+

Complete Prenatal Supplement
with 90mg iron

Unit Dose Pack
30 Softgel Capsules

RX
DIETARY SUPPLEMENT
U.S. Patent Pending